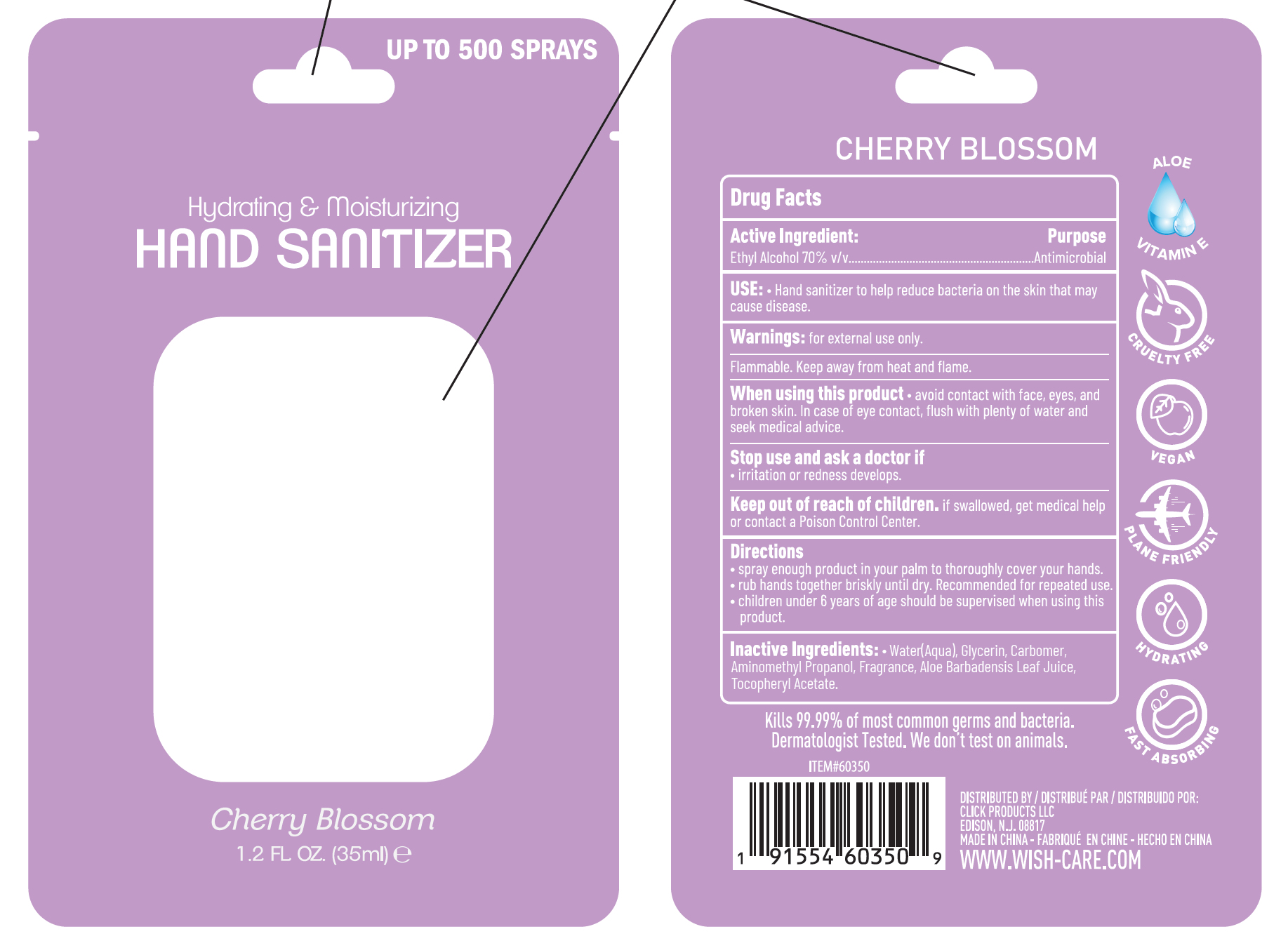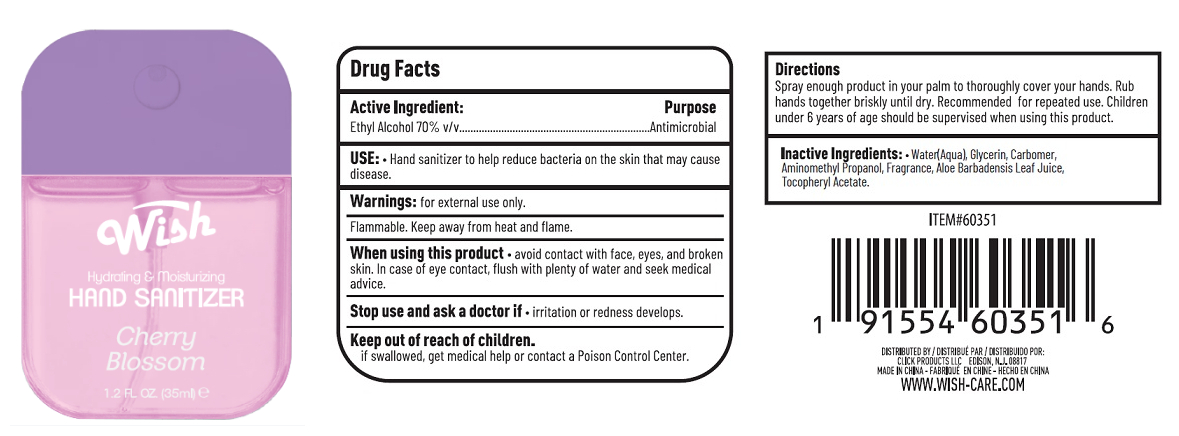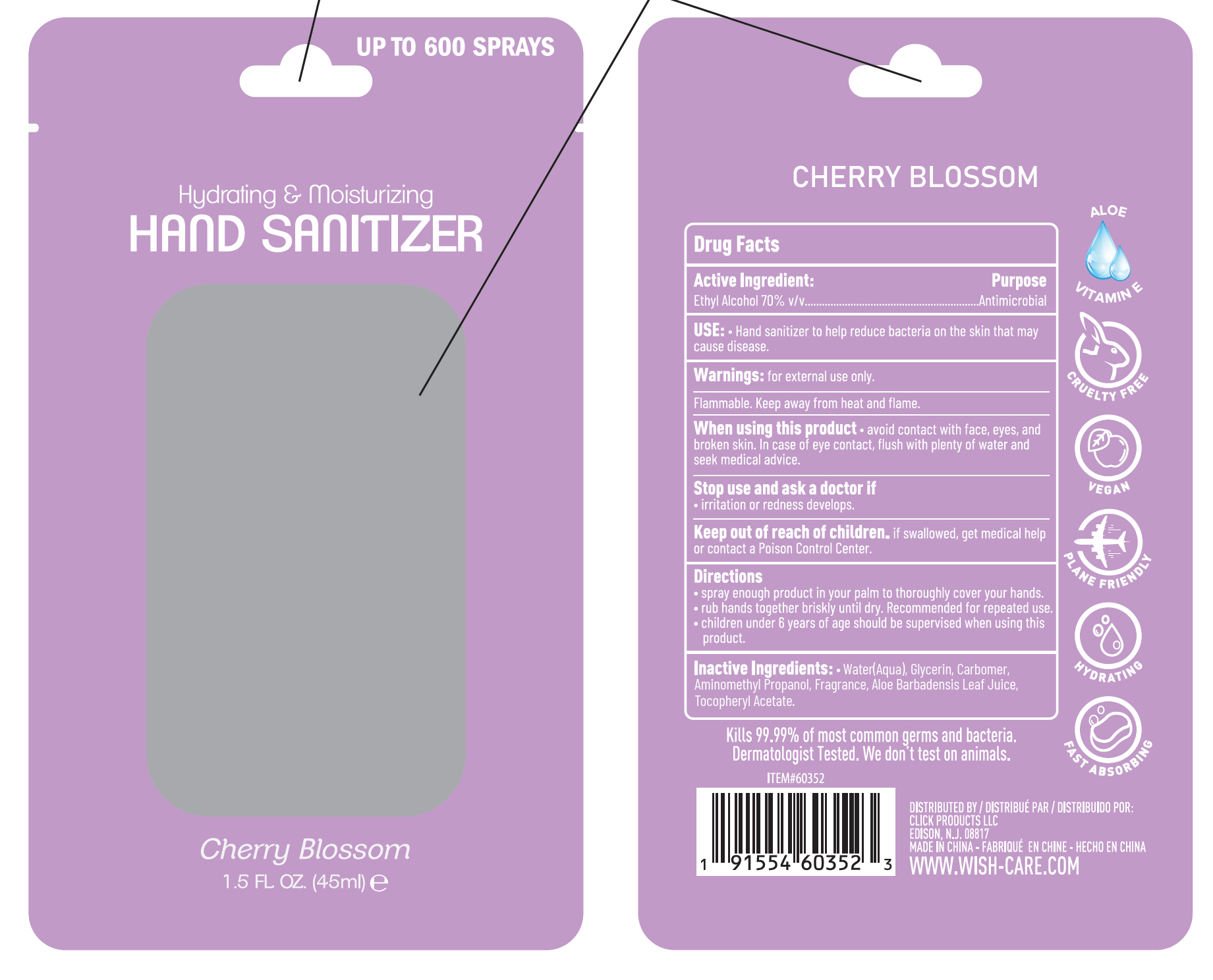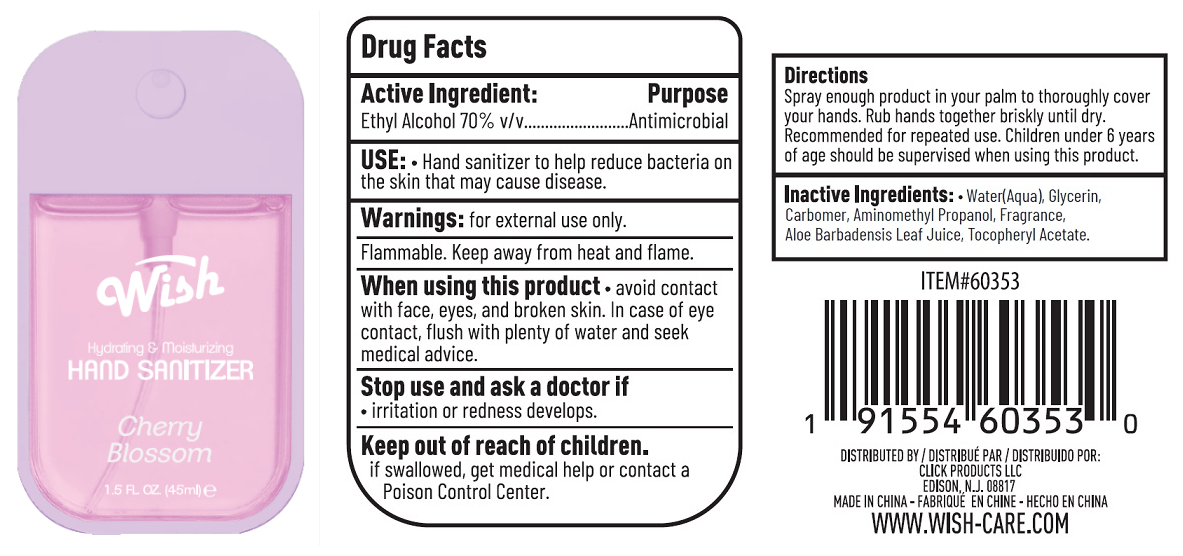 DRUG LABEL: WISH HAND SANITIZER CHERRY BLOSSOM
NDC: 71611-096 | Form: GEL
Manufacturer: CLICK PRODUCTS LLC
Category: otc | Type: HUMAN OTC DRUG LABEL
Date: 20240628

ACTIVE INGREDIENTS: ALCOHOL 70 mL/100 mL
INACTIVE INGREDIENTS: GLYCERIN; CARBOMER HOMOPOLYMER, UNSPECIFIED TYPE; AMINOMETHYLPROPANOL; .ALPHA.-TOCOPHEROL ACETATE; ALOE VERA LEAF; WATER

71611-096 WISH HAND SANITIZER CHERRY BLOSSOM

Active Ingredient:

Ethyl Alcohol 70% v/v

Purpose

Antimicrobial

INDICATIONS AND USAGE

USE: · Hand sanitizer to help reduce bacteria on the skin that may cause disease.

Warnings: for external use only.

Flammable. Keep away from heat and flame.

When using this product · avoid contact with face, eyes and broken skin. In case of eye contact, flush with plenty of water and seek medical advice.

Stop use and ask a doctor if

· irritation or redness develops.

Keep out of reach of children. if swallowed, get medical help or contact a poison control center.

Directions

· spray enough product in your palm to thoroughly cover your hands.

· rub hands together briskly until dry. Recommended for repeated use.

· children under 6years of age should be supervised when using this product.

INACTIVE INGREDIENT

Inactive Ingredients: · Water(Aqua), Glycerin, Carbomer, Aminomethyl Propanol, Fragrance, Aloe Barbadensis Leaf Juice, Tocopheryl Acetate.

PACKAGE LABEL

ITEM#60350
Cherry Blossom
1.2 FL OZ. (35ml)
NDC: 71611-096-01

PACKAGE LABEL

ITEM#60351
Cherry Blossom
1.2 FL OZ. (35ml)
NDC: 71611-096-02

PACKAGE LABEL

ITEM#60352
Cherry Blossom
1.5 FL OZ. (45ml)
NDC: 71611-096-03

PACKAGE LABEL

ITEM#60353
Cherry Blossom
1.5 FL OZ. (45ml)
NDC: 71611-096-04